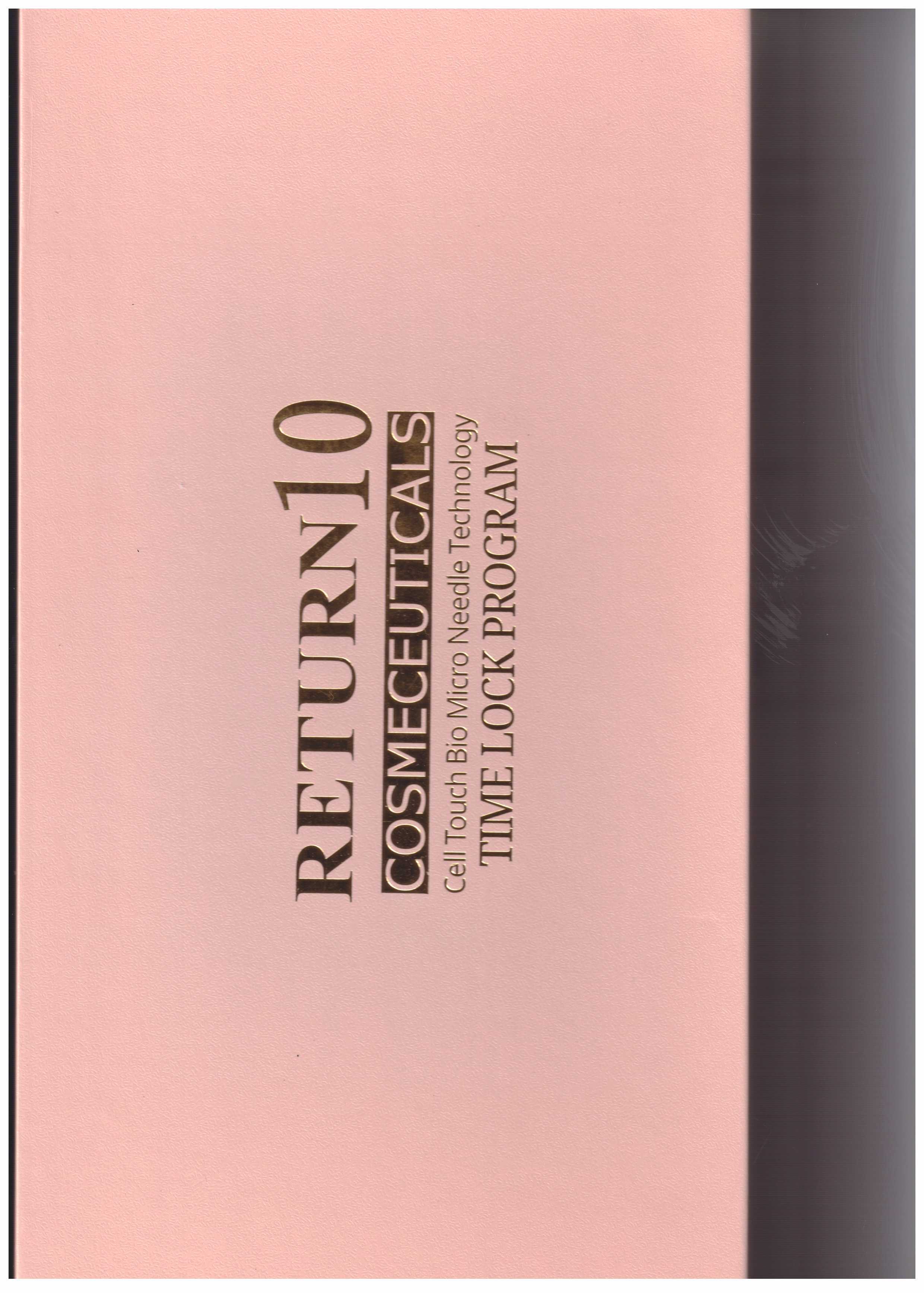 DRUG LABEL: Return 10 TIME LOCK PROGRAM
NDC: 72368-0009 | Form: KIT | Route: TOPICAL
Manufacturer: Threedayslove Co., Ltd.
Category: otc | Type: HUMAN OTC DRUG LABEL
Date: 20200106

ACTIVE INGREDIENTS: ADENOSINE 0.04 g/100 mL; NIACINAMIDE 3 g/100 mL; ADENOSINE 0.04 g/100 mL
INACTIVE INGREDIENTS: DIMETHICONE; BUTYLENE GLYCOL; BUTYLENE GLYCOL

Drug Facts

ACTIVE INGREDIENT

Adenosine, niacinamide

INACTIVE INGREDIENT

water, butylene glycol, etc.

PURPOSE

increase skin metabilism, it lasts for 72 hours in the pores

keep out of reach of the children

INDICATIONS AND USAGE

Take an appropriate amount to the skin

WARNINGS

Warning: 1. Do not use if you have any of following problems during use:

① Rash, red spots, swelling, irritation

② If the application site has any of the above problems due to direct sunlight

DOSAGE AND ADMINISTRATION

for external use only